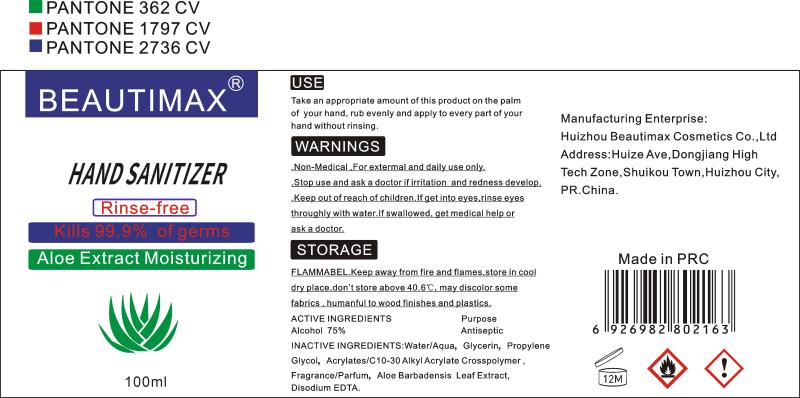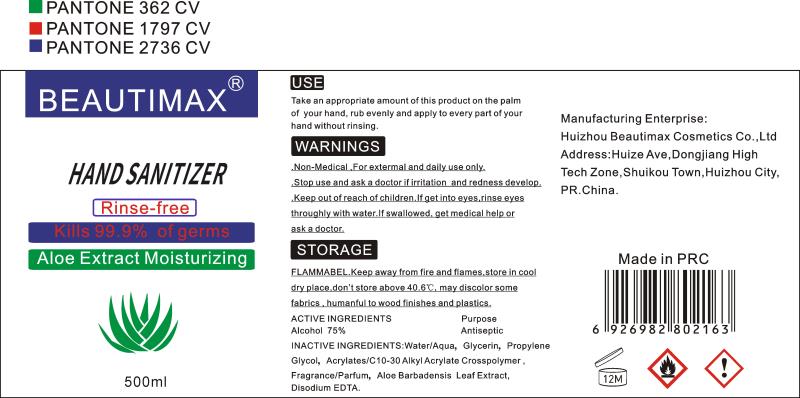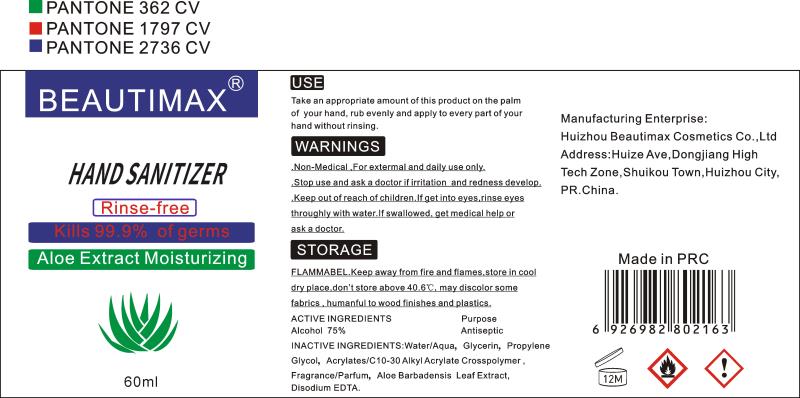 DRUG LABEL: BEAUTIMAX HAND SANITIZER
NDC: 76715-006 | Form: GEL
Manufacturer: Huizhou Beautimax Cosmetics Co. LTD
Category: otc | Type: HUMAN OTC DRUG LABEL
Date: 20200514

ACTIVE INGREDIENTS: ALCOHOL 75 mL/100 mL
INACTIVE INGREDIENTS: GLYCERIN 2 mL/100 mL; PROPYLENE GLYCOL 0.2 mL/100 mL; WATER 21.05 mL/100 mL; CARBOMER INTERPOLYMER TYPE A (ALLYL SUCROSE CROSSLINKED) 0.5 mL/100 mL; ALOE VERA LEAF 0.1 mL/100 mL; ORANGE 0.1 mL/100 mL; EDETATE DISODIUM 0.05 mL/100 mL

HAND SANITIZER

Active Ingredient(s)

Alcohol 75%

Purpose

Antiseptic, Hand Sanitizer

Use

Hand Sanitizer to help reduce bacteria that potentially can cause disease. For use when soap and water are not available.

Warnings

Non-medical For extemmaland dally use only. Stop use and ask a doctor imitation and redness develop,. Keep out reach of children, If get into eyes,rinse eyesthroughly with water If swallowed, get medical help or ask.

Do not use

- Stop use and ask a doctor imitation and redness develop

WHEN USING

/

Stop use and ask a doctor imitation and redness develop

KEEP OUT OF REACH OF CHILDREN

Keep out reach of children, If get into eyes,rinse eyesthroughly with water If swallowed, get medical help or ask..

Directions

/

Other information

store in cooldry place dont store ahoye., may discolor somefabrics.humanfulto wood and plastics

Inactive ingredients

Water/Aqua, Glycerin, PropyleneGlycol, Acrylates/C10-30 Alkyl Acrylate CrosspolymetFragrance/Parfum, Aloe Barbadensis Leaf ExtractDisodium EDTA